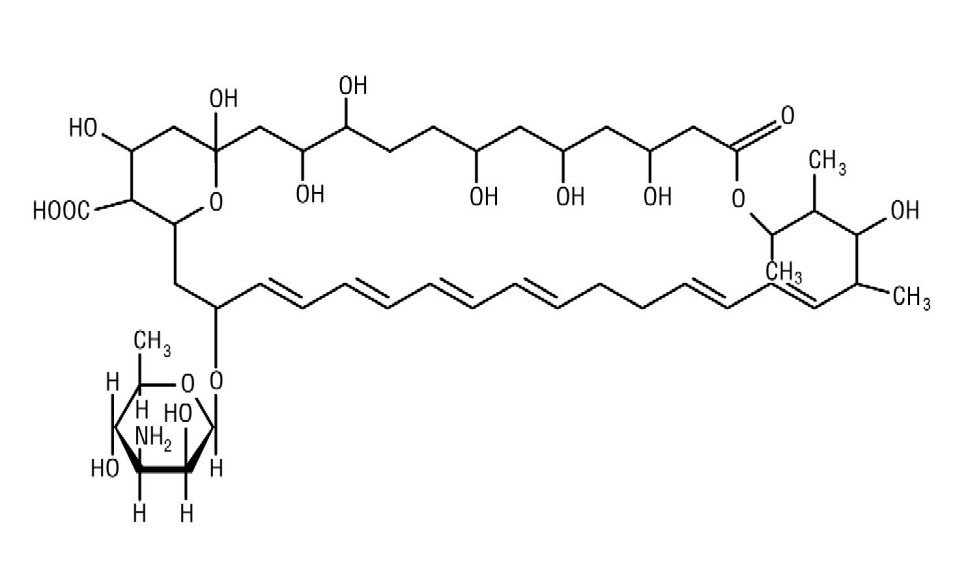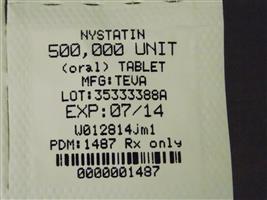 DRUG LABEL: Nystatin
NDC: 68151-1487 | Form: TABLET, FILM COATED
Manufacturer: Carilion Materials Management
Category: prescription | Type: HUMAN PRESCRIPTION DRUG LABEL
Date: 20131015

ACTIVE INGREDIENTS: NYSTATIN 500000 [USP'U]/1 1
INACTIVE INGREDIENTS: STARCH, CORN; POVIDONE K29/32; CELLULOSE, MICROCRYSTALLINE; SODIUM STARCH GLYCOLATE TYPE A POTATO; TALC; MAGNESIUM STEARATE; WATER; ISOPROPYL ALCOHOL

NYSTATIN TABLETS USP 0983 Rx only

DESCRIPTION

Nystatin is an antimycotic polyene antibiotic obtained from . Its structural formula: Streptomyces noursei

C H NO M.W. 926.13477517

Nystatin tablets contain the inactive ingredients: Corn Starch, Povidone, Compressible Sugar, Microcrystalline Cellulose, Sodium Starch Glycolate, Talc, Magnesium Stearate, Purified Water, and Coloring.

CLINICAL PHARMACOLOGY

Pharmacokinetics

Gastrointestinal absorption of nystatin is insignificant. Most orally administered nystatin is passed unchanged in the stool. In patients with renal insufficiency receiving oral therapy with conventional dosage forms, significant plasma concentrations of nystatin may occasionally occur.

Microbiology

Nystatin is both fungistatic and fungicidal against a wide variety of yeasts and yeast like fungi. demonstrates no significant resistance to nystatin on repeated subculture in increasing levels of nystatin; other species become quite resistant. Generally, resistance does not develop . Nystatin acts by binding to sterols in the cell membrane of susceptible species with a resultant change in membrane permeability allowing leakage of intracellular components. Nystatin exhibits no appreciable activity against bacteria, protozoa, or viruses. in vitro Candida albicansin vitro Candidain vivo Candida

INDICATIONS AND USAGE

Nystatin Tablets are intended for the treatment of non-esophageal mucus membrane gastrointestinal candidiasis.

CONTRAINDICATIONS

Nystatin Tablets are contraindicated in patients with a history of hypersensitivity to any of their components.

PRECAUTIONS

General

This medication is not to be used for the treatment of systemic mycoses. Discontinue treatment if sensitization or irritation is reported during use.

Carcinogenesis, Mutagenesis, Impairment of Fertility

No long-term animal studies have been performed to evaluate carcinogenic potential. There also have been no studies to determine mutagenicity or whether this medication affects fertility in males or females.

Pregnancy

Teratogenic Effects

Pregnancy category C

Animal reproduction studies have not been conducted with nystatin. It is also not known whether nystatin can cause fetal harm when administered to a pregnant woman or can affect reproduction capacity. Nystatin should be given to a pregnant woman only if clearly needed.

Nursing Mothers

It is not known whether nystatin is excreted in human milk. Because many drugs are excreted in human milk, caution should be exercised when nystatin is administered to a nursing woman.

ADVERSE REACTIONS

Nystatin is well tolerated even with prolonged therapy. Oral irritation and sensitization have been reported (see). PRECAUTIONS, General

Gastrointestinal

Diarrhea (including one case of bloody diarrhea), nausea, vomiting, gastrointestinal upset/disturbances.

Dermatologic

Rash, including urticaria has been reported rarely. Stevens-Johnson syndrome has been reported very rarely.

Other

Tachycardia, bronchospasm, facial swelling, and nonspecific myalgia have also been rarely reported.

OVERDOSAGE

Oral doses of nystatin in excess of five million units daily have caused nausea and gastrointestinal upset. There have been no reports of serious toxic effects of superinfections (see). CLINICALPHARMACOLOGY, Pharmacokinetics

DOSAGE AND ADMINISTRATION

The usual therapeutic dosage is one to two tablets (500,000 to 1,000,000 units nystatin) three times daily. Treatment should generally be continued for at least 48 hours after clinical cure to prevent relapse.

HOW SUPPLIED

NDC:68151-1487-0 in a PACKAGE of 1 TABLET, FILM COATEDS

Nystatin 500,000 units

Nystatin Tablets USP 500,000 units (Oral) 100 Label Text

0093- -01 NDC 0983

NYSTATIN
Tablets USP
500,000 units (oral)

Rx only

100 TABLETS

TEVA